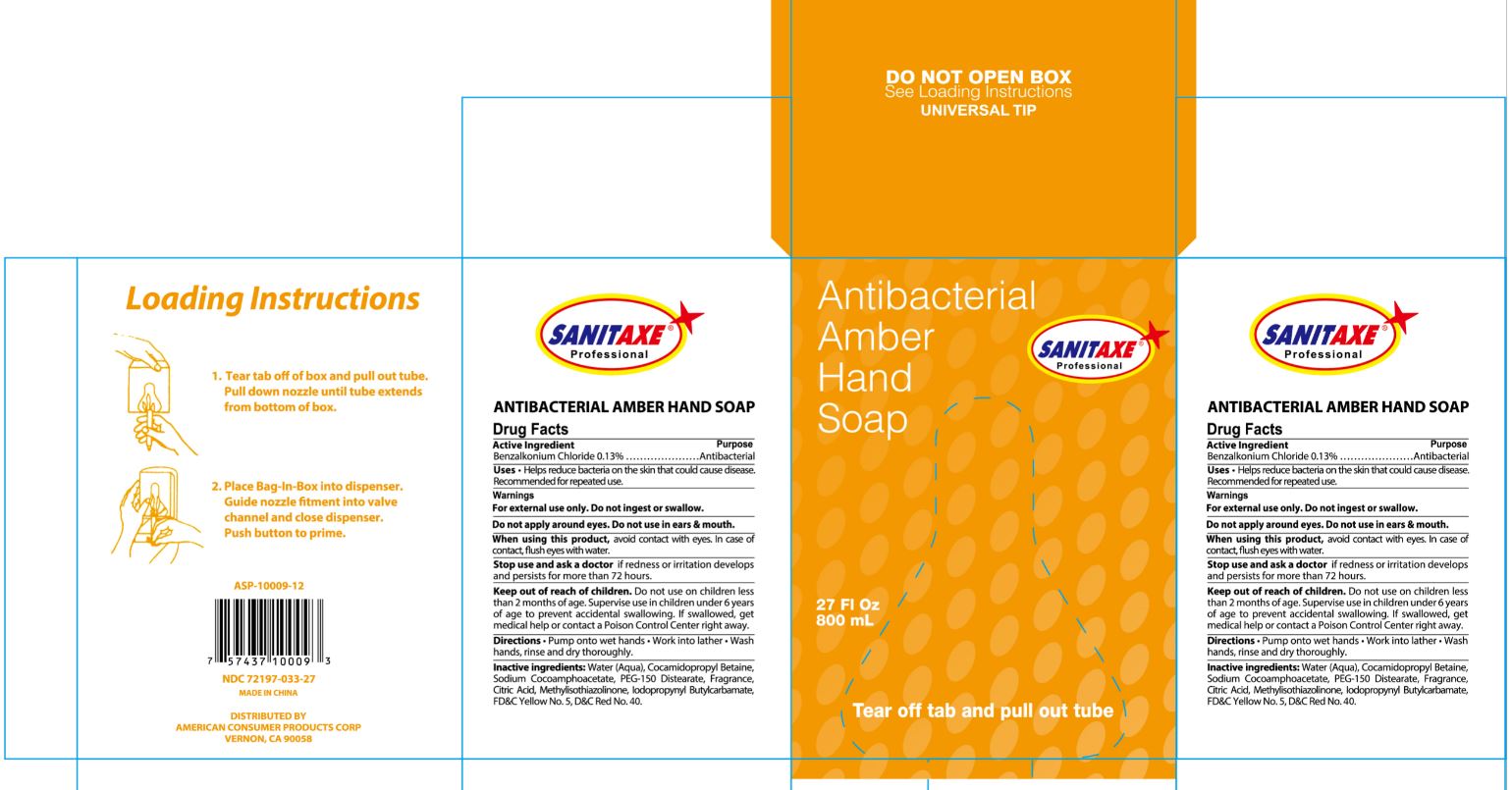 DRUG LABEL: Sanitaxe Antibacterial
NDC: 72197-033 | Form: GEL
Manufacturer: American Consumer Products Corp
Category: otc | Type: HUMAN OTC DRUG LABEL
Date: 20250123

ACTIVE INGREDIENTS: BENZALKONIUM CHLORIDE 0.13 g/100 mL
INACTIVE INGREDIENTS: FD&C YELLOW NO. 5; FD&C RED NO. 40; WATER; METHYLISOTHIAZOLINONE; IODOPROPYNYL BUTYLCARBAMATE; PEG-150 DISTEARATE; ANHYDROUS CITRIC ACID; COCAMIDOPROPYL BETAINE; SODIUM COCOAMPHOACETATE

Sanitaxe Hand Soap

Active Ingredient

Benzalkonium Chloride .13%

Purpose

Antiseptic

Uses

Uses ● Helps reduce bacteria on the skin that could cause disease. Recommended for repeated use.

Warnings

Warnings – For external use only. Do not ingest or swallow.

Do not apply around eyes. Do not use in ears & mouth.

When using this product, avoid contact with eyes. In case of contact, flush eyes with water.

Stop use and ask a doctor if redness or irritation develops and persists for more than 72 hours.

Keep out of reach of children. Do not use on children less than 2 months of age.

Supervise use in children under 6 years of age to prevent accidental swallowing.

If swallowed, get medical help or contact a Poison Control Center right away.

Directions

Directions ● Pump onto wet hands ● Work into lather ● Wash hands, rinse and dry thoroughly.

Inactive ingredients

Inactive ingredients: Water (Aqua), Cocamidopropyl Betaine, Sodium Cocoamphoacetate, PEG-150 Disterate, Fragrance, Citric Acid, Methylisothiazolinone, Iodopropynyl Butylcarbamate, FD&C Yellow No. 5, D&C Red No. 33.